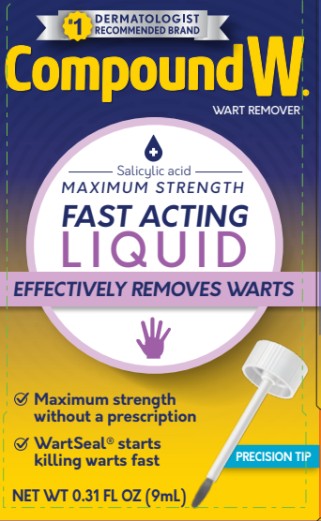 DRUG LABEL: Compound W
NDC: 63029-597 | Form: LIQUID
Manufacturer: Medtech Products Inc.
Category: otc | Type: HUMAN OTC DRUG LABEL
Date: 20250808

ACTIVE INGREDIENTS: SALICYLIC ACID 150 mg/1 mL
INACTIVE INGREDIENTS: ALCOHOL; CAMPHOR (NATURAL); CASTOR OIL; LYTTA VESICATORIA; ETHER; ETHYLCELLULOSES; HYPOPHOSPHOROUS ACID; MENTHOL; POLYSORBATE 80

Compound W Liquid - First Aid

Compound W Liquid
Salicylic Acid WART REMOVER
MAXIMUM STRENGTH
FAST ACTING LIQUID
NET WT 0.31 FL OZ (9 mL)

Drug Facts

Active ingredient

Salicylic acid 17% w/w

Purpose

Wart remover

Use

- for the removal of common and plantar warts
- the common wart is easily recognized by the rough “cauliflower-like” appearance of the surface. the plantar wart is recognized by its location only on the bottom of the foot, its tenderness and the interruption of the footprint pattern

Warnings

For external use only

Flammable. Keep away from fire and flame.

Do not use

- on irritated skin or on any area that is infected or reddened
- on moles, birthmarks, warts with hair growing from them, genital warts or warts on the face or mucous membranes
- if you have diabetes or poor blood circulation

When using this product

- avoid contact with eyes. If product gets into the eye, flush with water for 15 minutes.
- avoid inhaling vapors
- cap bottle tightly and store at room temperature away from heat

Keep out of reach of children.

If swallowed, get medical help or contact a Poison Control Center (1-800-222-1222) right away.

Directions

- wash affected area
- may soak wart in warm water for 5 minutes
- dry area thoroughly
- using applicator, apply one drop at a time to sufficiently cover each wart
- let dry
- repeat this procedure once or twice daily as needed (until wart is removed) for up to 12 weeks

Other information

- store at room temperature
- avoid excessive heat 37°C (99°F)
- skin discoloration may occur during or after use
- wipe the rim of the bottle with a paper towel between uses

Inactive ingredients

alcohol, camphor, castor oil, collodion, ether, ethylcellulose, hypophosphorous acid, menthol, polysorbate 80

Questions?

1-800-443-4908 CompoundW.com

PRINCIPAL DISPLAY PANEL

Compound W
Salicylic acid
Maximum Strength
Fast Acting Liquid
Net WT 0.31 FL OZ(9 mL)